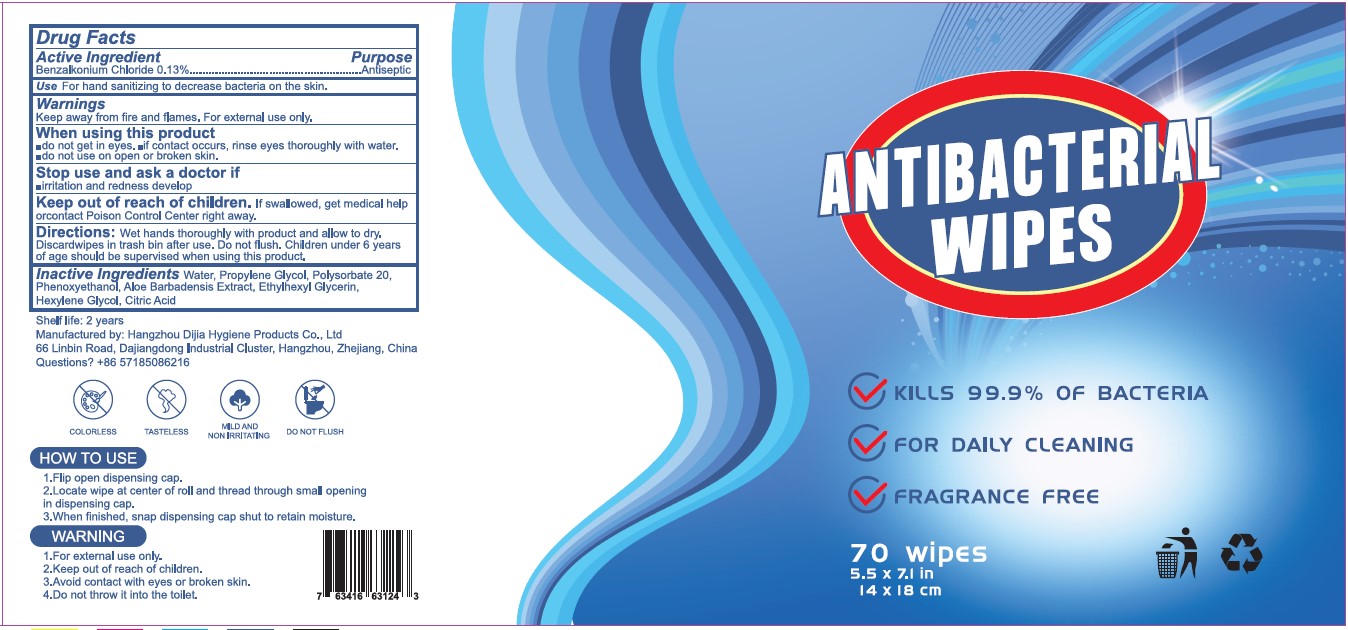 DRUG LABEL: ANTIBACTERIAL WIPES
NDC: 87931-003 | Form: CLOTH
Manufacturer: Hangzhou Dijia Hygiene Products Co.,Ltd
Category: otc | Type: HUMAN OTC DRUG LABEL
Date: 20201021

ACTIVE INGREDIENTS: BENZALKONIUM CHLORIDE 0.13 g/100 mL
INACTIVE INGREDIENTS: WATER; PROPYLENE GLYCOL; POLYSORBATE 20; PHENOXYETHANOL; ALOE VERA FLOWER; ETHYLHEXYLGLYCERIN; HEXYLENE GLYCOL; CITRIC ACID MONOHYDRATE

Active Ingredient

Benzalkonium 0.13% Purpose: Antiseptic

Purpose

Antiseptic

Use

For hand sanitizing to decrease bacteria on the skin.

Warnings

Keep away from fire and flames. For external use only.keep out of reach of children.avoid contact with eyes or broken skin.Do not throw it into the toilet.

do not use on open or broken skin

WHEN USING

do not get in eyes. if contact occurs, rinse eyes thoroughly with water.do not use on open or broken skin.

Stop use and ask a doctor if irritation and redness develop

Keep out of reach of children. If swallowed, get medical help or contact a Poison Control Center right away.

Directions

- Wet hands thoroughly with product and allow to dry.
  Discardwipes in trash bin after use. Do not flush. Children under 6 years
  of age should be supervised when using this product.

Inactive ingredients

Water, Propylene Glycol, Polysorbate 20,Phenoxyethano , Aloe Barbadensis Extract, Ethylhexyl Glycerin,Hexylene Glycol, Citric Acid